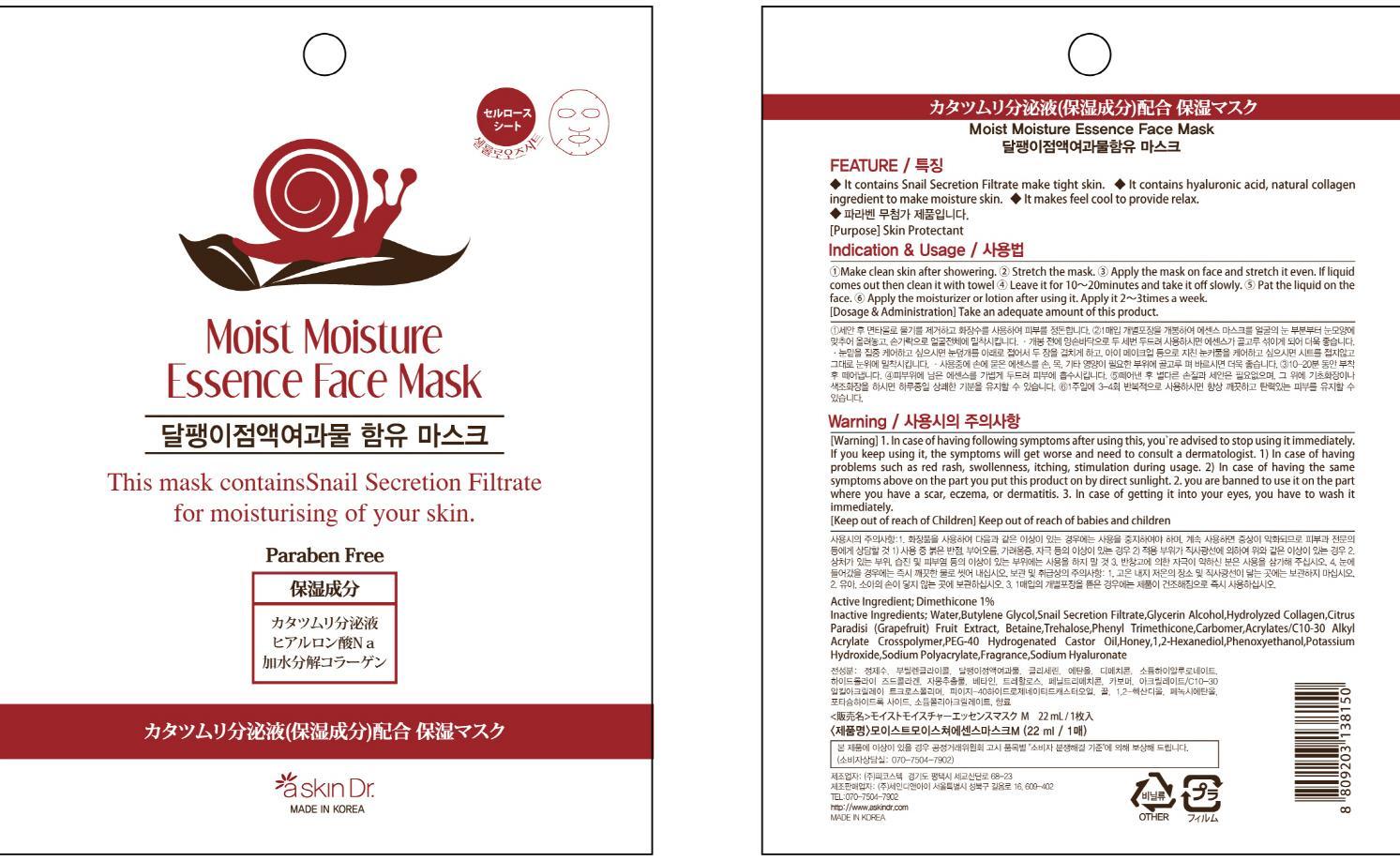 DRUG LABEL: MOIST MOISTURE ESSENCE FACE MASK
NDC: 69072-060 | Form: PATCH
Manufacturer: Seindni Co.,ltd
Category: otc | Type: HUMAN OTC DRUG LABEL
Date: 20181210

ACTIVE INGREDIENTS: Dimethicone 0.22 mg/22 mL
INACTIVE INGREDIENTS: Water; Butylene Glycol

ACTIVE INGREDIENT

Active Ingredients: Dimethicone 1%

INACTIVE INGREDIENT

Inactive Ingredients:
Water,Butylene Glycol,Snail Secretion Filtrate,Glycerin Alcohol,Hydrolyzed Collagen,Citrus Paradisi (Grapefruit) Fruit Extract, Betaine,Trehalose,Phenyl Trimethicone,Carbomer,Acrylates/C10-30 Alkyl Acrylate Crosspolymer,PEG-40 Hydrogenated Castor Oil,Honey,1,2-Hexanediol,Phenoxyethanol,Potassium Hydroxide,Sodium Polyacrylate,Fragrance,Sodium Hyaluronate

PURPOSE

Purpose: Skin Protectant

WARNINGS

Warning:
1. In case of having following symptoms after using this, you're advised to stop using it immediately. If you keep using it, the symptoms will get worse and need to consult a dermatologist. 1) In case of having problems such as red rash, swollenness, itching, stimulation during usage. 2) In case of having the same symptoms above on the part you put this product on by direct sunlight. 2. you are banned to use it on the part where you have a scar, eczema, or dermatitis. 3. In case of getting it into your eyes, you have to wash it immediately.

Keep out of reach of children: Keep out of reach of babies and children

INDICATIONS AND USAGE

Indication and Usage:
1. Make clean skin after showering.
2. Stretch the mask.
3. Apply the mask on face and stretch it even. If liquid comes out then clean it with towel.
4. Leave it for 10-20 minutes and take it off slowly.
5. Pat the liquid on the face.
6. Apply the moisturizer or lotion using it. Apply it 2-3 times a week.

Dosage and Administration: Take an adequate amount of this product.